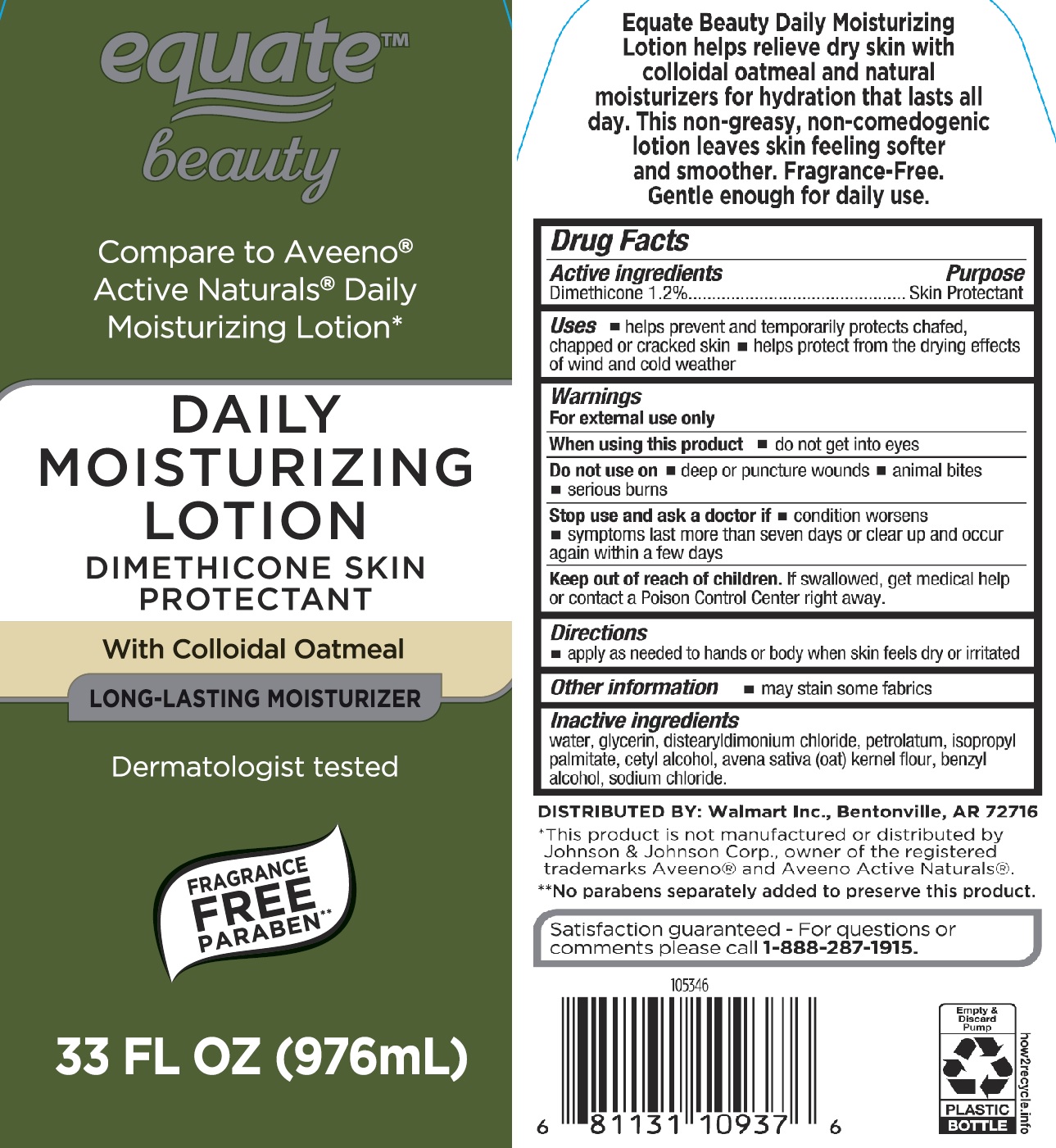 DRUG LABEL: Equate Daily Moisturizing Dimethicone Skin Protectant
NDC: 49035-575 | Form: LOTION
Manufacturer: Walmart Stores Inc.
Category: otc | Type: HUMAN OTC DRUG LABEL
Date: 20241016

ACTIVE INGREDIENTS: DIMETHICONE 12 mg/1 mL
INACTIVE INGREDIENTS: WATER; GLYCERIN; DISTEARYLDIMONIUM CHLORIDE; PETROLATUM; CETYL ALCOHOL; OATMEAL; BENZYL ALCOHOL; SODIUM CHLORIDE; ISOPROPYL PALMITATE

Equate Daily Moisturizing Dimethicone Skin Protectant

Active ingredients

Dimethicone 1.2%

Purpose

Skin Protectant

Uses

- helps prevent and temporarily protects chafed, chapped or cracked skin
- helps protect from the drying effects of wind and cold weather

Warnings

When using this product • do not get into eyes

Do not use on

- deep or puncture wounds
- animal bites
- serious burns

Stop use and ask a doctor if

- condition worsens
- symptoms last more than seven days or clear up and occur again within a few days

Keep out of reach of children.

If swallowed, get medical help or contact a Poison Control Center right away.

Directions

- apply as needed to hands or body when skin feels dry or irritated

Other information

may stain some fabrics

Inactive ingredients

water, glycerin, distearyldimonium chloride, petrolatum, isopropyl palmitate, cetyl alcohol, avena sativa (oat) kernel flour, benzyl alcohol, sodium chloride.

PACKAGE LABEL

Equate Daily Moisturizing Dimethicone Skin Protectant